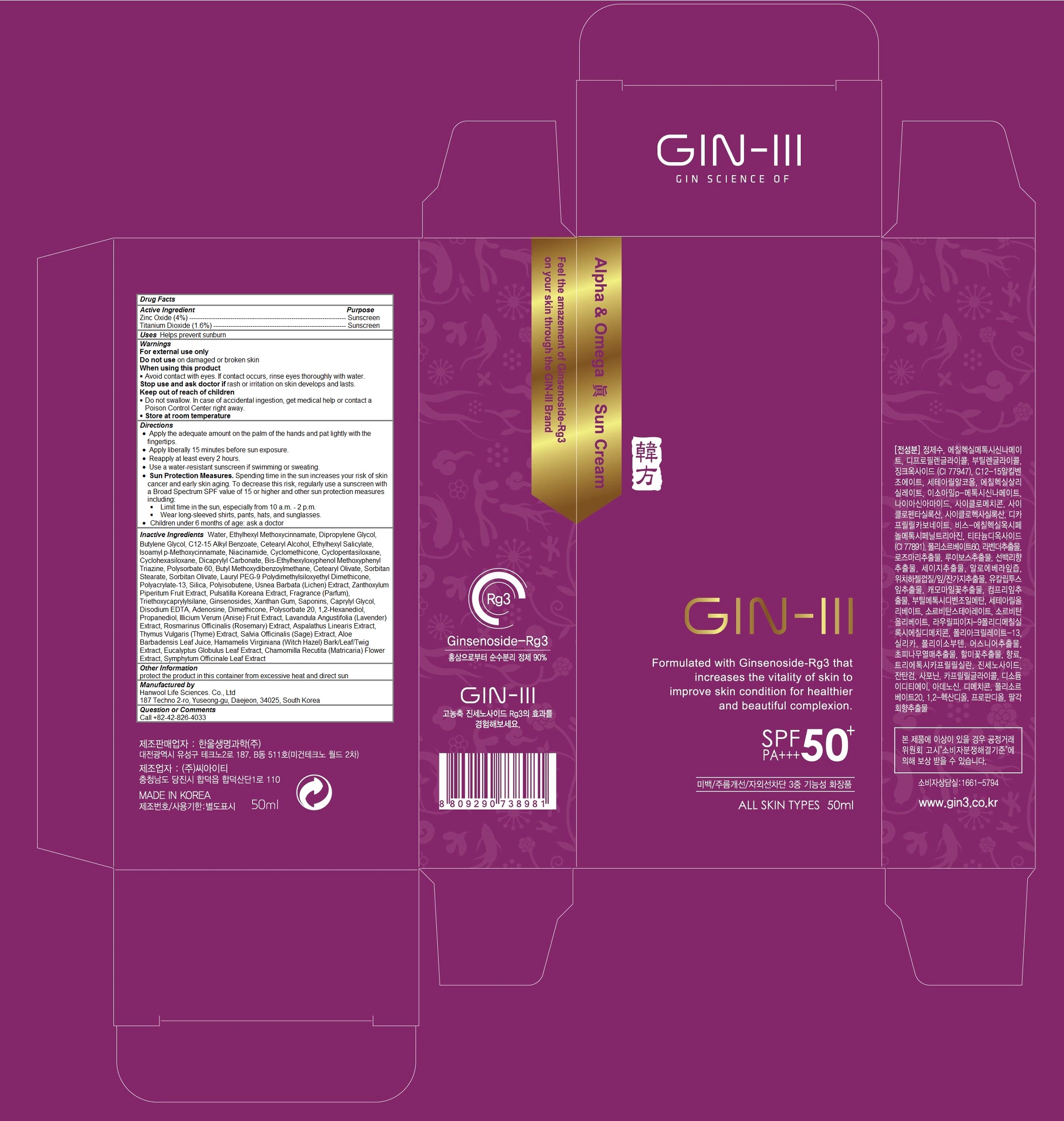 DRUG LABEL: GIN-III Alpha and Omega GIN Sun
NDC: 71135-100 | Form: CREAM
Manufacturer: Hanwool Life Sciences. Co., Ltd
Category: otc | Type: HUMAN OTC DRUG LABEL
Date: 20161228

ACTIVE INGREDIENTS: ZINC OXIDE 2 g/50 mL; TITANIUM DIOXIDE 0.8 g/50 mL
INACTIVE INGREDIENTS: WATER; OCTINOXATE; DIPROPYLENE GLYCOL; Butylene Glycol; ALKYL (C12-15) BENZOATE; CETOSTEARYL ALCOHOL; OCTISALATE; AMILOXATE; Niacinamide; Cyclomethicone; CYCLOMETHICONE 5; DICAPRYLYL CARBONATE; BEMOTRIZINOL; Polysorbate 60; AVOBENZONE; Cetearyl Olivate; SORBITAN MONOSTEARATE; SORBITAN OLIVATE; LAURYL PEG-9 POLYDIMETHYLSILOXYETHYL DIMETHICONE; SILICON DIOXIDE; POLYISOBUTYLENE (1000 MW); USNEA BARBATA; ZANTHOXYLUM PIPERITUM FRUIT PULP; PULSATILLA KOREANA ROOT; TRIETHOXYCAPRYLYLSILANE; GINSENOSIDES; Xanthan Gum; Caprylyl Glycol; EDETATE DISODIUM ANHYDROUS; Adenosine; Dimethicone; Polysorbate 20; 1,2-Hexanediol; Propanediol; STAR ANISE FRUIT; LAVANDULA ANGUSTIFOLIA FLOWERING TOP; ROSEMARY; ASPALATHUS LINEARIS WHOLE; THYME; SALVIA OFFICINALIS ROOT; ALOE VERA LEAF; HAMAMELIS VIRGINIANA TOP; EUCALYPTUS GLOBULUS LEAF; CHAMOMILE; COMFREY LEAF

GIN-III Alpha and Omega GIN Sun Cream

Active Ingredients

Zinc Oxide (4%)

Titanium Dioxide (1.6%)

Purpose

Sunscreen

Keep out of reach of children

 Do not swallow. In case of accidental ingestion, get medical help or contact a Poison Control Center right away.

Warnings

For external use only
Do not use on damaged or broken skin
When using this product
 Avoid contact with eyes. If contact occurs, rinse eyes thoroughly with water.
Stop use and ask doctor if rash or irritation on skin develops and lasts.

 Store at room temperature

Directions

Apply the adequate amount on the palm of the hands and pat lightly with the fingertips.
• Apply liberally 15 minutes before sun exposure.
• Reapply at least every 2 hours.
• Use a water-resistant sunscreen if swimming or sweating.
• Sun Protection Measures. Spending time in the sun increases your risk of skin cancer and early skin aging. To decrease this risk, regularly use a sunscreen with a Broad Spectrum SPF value of 15 or higher and other sun protection measures including:
 Limit time in the sun, especially from 10 a.m. - 2 p.m.
 Wear long-sleeved shirts, pants, hats, and sunglasses.
• Children under 6 months of age: ask a doctor

Uses

Helps prevent sunburn

Inactive Ingredients

Water, Ethylhexyl Methoxycinnamate, Dipropylene Glycol, Butylene Glycol, C12-15 Alkyl Benzoate, Cetearyl Alcohol, Ethylhexyl Salicylate, Isoamyl p-Methoxycinnamate, Niacinamide, Cyclomethicone, Cyclopentasiloxane, Cyclohexasiloxane, Dicaprylyl Carbonate, Bis-Ethylhexyloxyphenol Methoxyphenyl Triazine, Polysorbate 60, Butyl Methoxydibenzoylmethane, Cetearyl Olivate, Sorbitan Stearate, Sorbitan Olivate, Lauryl PEG-9 Polydimethylsiloxyethyl Dimethicone, Polyacrylate-13, Silica, Polyisobutene, Usnea Barbata (Lichen) Extract, Zanthoxylum Piperitum Fruit Extract, Pulsatilla Koreana Extract, Fragrance (Parfum), Triethoxycaprylylsilane, Ginsenosides, Xanthan Gum, Saponins, Caprylyl Glycol, Disodium EDTA, Adenosine, Dimethicone, Polysorbate 20, 1,2-Hexanediol, Propanediol, Illicium Verum (Anise) Fruit Extract, Lavandula Angustifolia (Lavender) Extract, Rosmarinus Officinalis (Rosemary) Extract, Aspalathus Linearis Extract, Thymus Vulgaris (Thyme) Extract, Salvia Officinalis (Sage) Extract, Aloe Barbadensis Leaf Juice, Hamamelis Virginiana (Witch Hazel) Bark/Leaf/Twig Extract, Eucalyptus Globulus Leaf Extract, Chamomilla Recutita (Matricaria) Flower Extract, Symphytum Officinale Leaf Extract